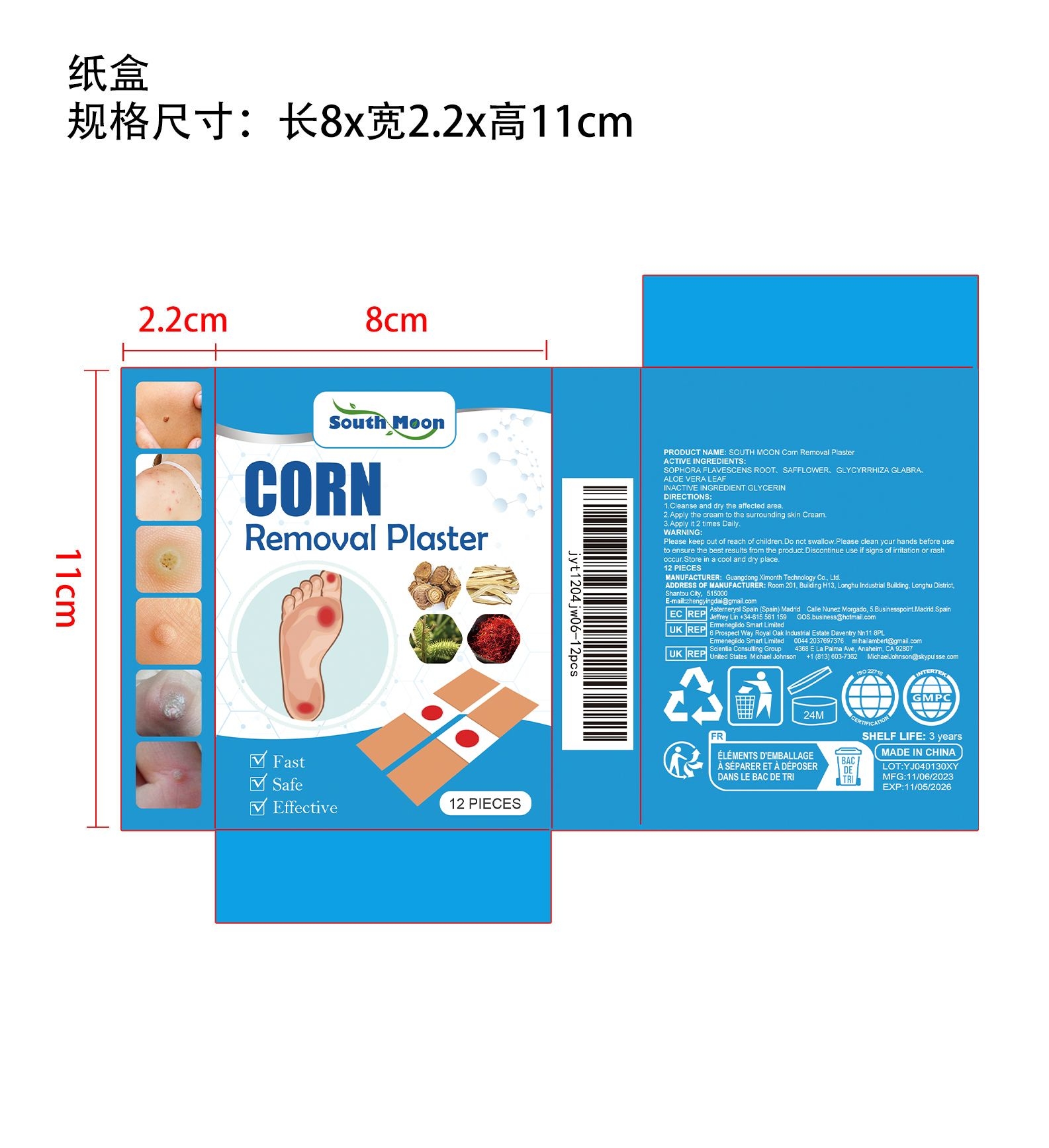 DRUG LABEL: SOUTH MOON Corn Removal Plaster
NDC: 84660-062 | Form: PLASTER
Manufacturer: Guangdong Ximonth Technology Co., Ltd.
Category: otc | Type: HUMAN OTC DRUG LABEL
Date: 20241102

ACTIVE INGREDIENTS: GLYCYRRHIZA GLABRA 2 g/16 g; SAFFLOWER 4 g/16 g; ALOE VERA LEAF 2 g/16 g; SOPHORA FLAVESCENS ROOT 4 g/16 g
INACTIVE INGREDIENTS: GLYCERIN 4 g/16 g

Active Ingredient(s)

SOPHORA FLAVESCENS ROOT、SAFFLOWER、GLYCYRRHIZA GLABRA、ALOE VERA LEAF

Use

1.Cleanse and dry the affected area.
2.Apply the cream to the surrounding skin Cream.
3.Apply it 2 times Daily.

Warnings

Please keep out of reach of children.Do not swallow.Please clean your hands before use to ensure the best results from the product.Discontinue use if signs of irritation or rash occur.Store in a cool and dry place.

Do not use

Discontinue use if signs of irritation or rash occur.

Stop Use

Discontinue use if signs of irritation or rash occur.

KEEP OUT OF REACH OF CHILDREN

Please keep out of reach of children. Do not swallow.

STORAGE AND HANDLING

Store in a cool and dry place.

INACTIVE INGREDIENT

GLYCERIN